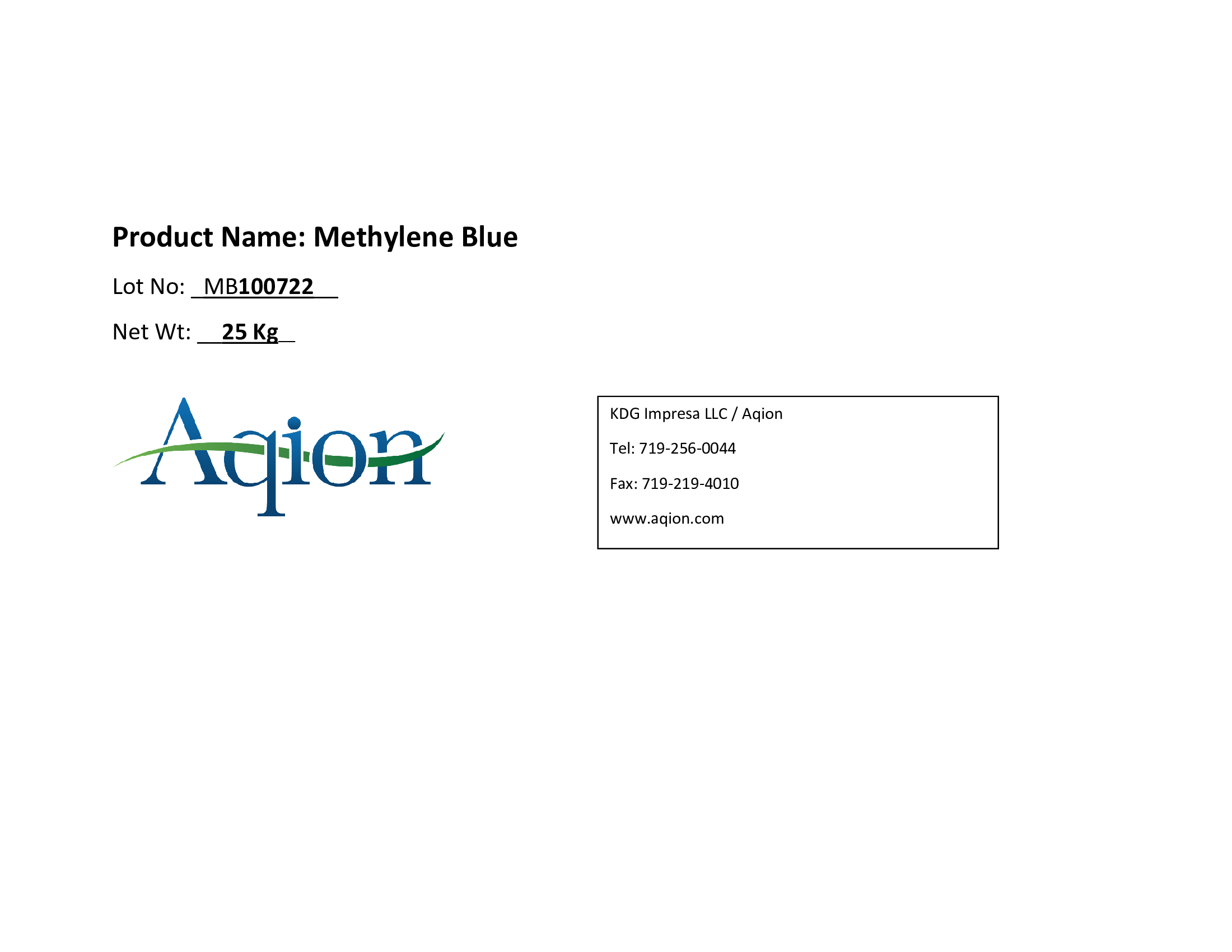 DRUG LABEL: Methylene Blue
NDC: 43457-653 | Form: CRYSTAL
Manufacturer: KDG Impresa LLC, Aqion
Category: other | Type: BULK INGREDIENT - ANIMAL DRUG
Date: 20231207

ACTIVE INGREDIENTS: METHYLENE BLUE 1 kg/1 kg

Methylene Blue